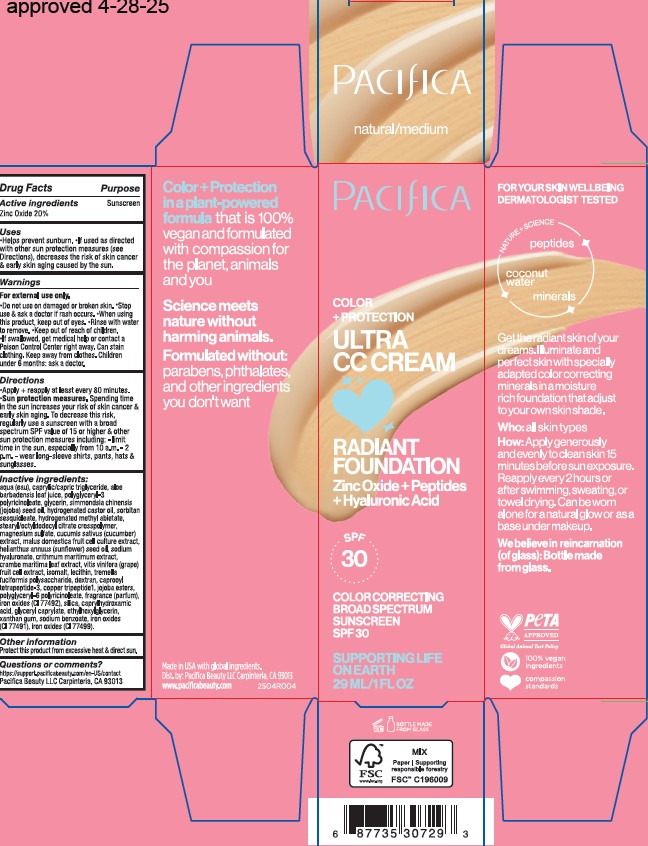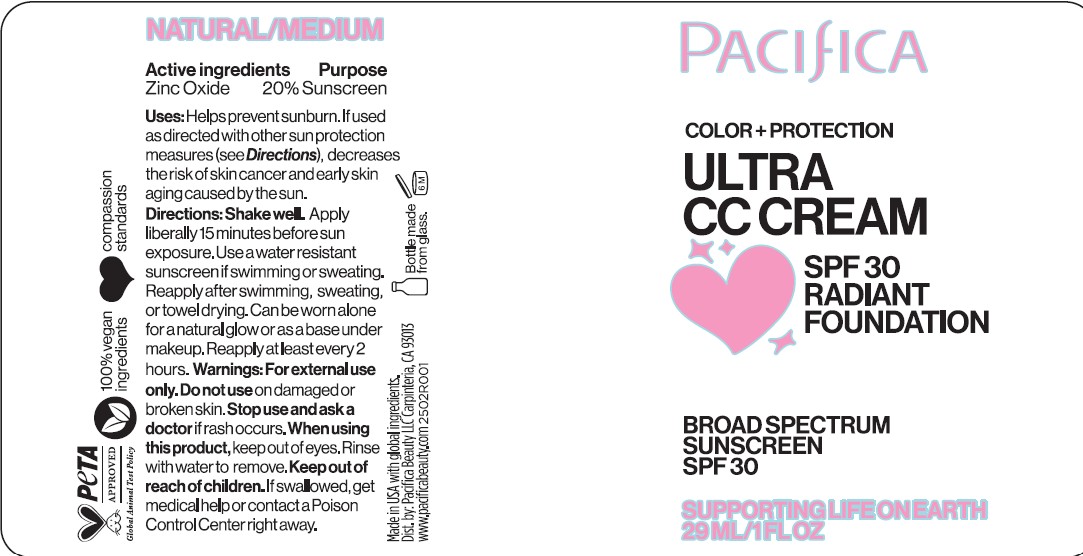 DRUG LABEL: Zinc Oxide
NDC: 61197-315 | Form: CREAM
Manufacturer: Pacifica Beauty, LLC
Category: otc | Type: HUMAN OTC DRUG LABEL
Date: 20250610

ACTIVE INGREDIENTS: ZINC OXIDE 20 mg/100 mL
INACTIVE INGREDIENTS: GLYCERIN; MAGNESIUM SULFATE; MALUS DOMESTICA FLOWER; HELIANTHUS ANNUUS (SUNFLOWER) SEED OIL; SODIUM HYALURONATE; CRITHMUM MARITIMUM; SILICA; CAPRYLHYDROXAMIC ACID; XANTHAN GUM; CAPROOYL TETRAPEPTIDE-3; POLYGLYCERYL-6 POLYRICINOLEATE; TREMELLA FUCIFORMIS WHOLE; DEXTRAN 1; CI 77491; HYDROGENATED CASTOR OIL; HYDROGENATED METHYL ABIETATE; HYDROLYZED JOJOBA ESTERS; CI 77492; ALOE BARBADENSIS LEAF JUICE; SODIUM BENZOATE; SORBITAN SESQUIOLEATE; STEARYL/OCTYLDODECYL CITRATE CROSSPOLYMER; CUCUMIS SATIVUS (CUCUMBER) FRUIT; CRAMBE MARITIMA LEAF; WATER; CAPRYLIC/CAPRIC TRIGLYCERIDE; POLYGLYCERYL-3 RICINOLEATE; SIMMONDSIA CHINENSIS (JOJOBA) SEED OIL; ETHYLHEXYLGLYCERIN; CI 77499; VITIS VINIFERA FRUIT OIL; ISOMALT; LECITHIN, SOYBEAN; COPPER TRIPEPTIDE-1; GLYCERYL CAPRYLATE

Pacifica Ultra CC Cream Radiant Foundation SPF 30 Natural/Medium

Active ingredients

Zinc Oxide 20%

Purpose

Sunscreen

Uses

Helps prevent sunburn. If used as directed with other sun protection measures (see Directions), decreases the risk of skin cancer & early skin aging caused by the sun.

Warnings

For external use only. Do not use on damaged or broken skin. Stop use & ask a doctor if rash occurs. When using this product, keep out of eyes. Rinse with water to remove. Keep out of reach of children. If swallowed, get medical help or contact a Poison Control Center right away. Can stain clothing. Keep away from clothes. Children under 6 months: ask a doctor.

Keep out of reach of children

Directions

Apply + reapply at least every 80 minutes. Sun protection measures. Spending time in the sun increases your risk of skin cancer & early skin aging. To decrease this risk, regularly use a sunscreen with a broad spectrum SPF value of 15 or higher & other sun protection measures including: -limit time in the sun, especially from 10 a.m. - 2 p.m. -wear long-sleeve shirts, pants, hats & sunglasses.

Inactive ingredients

aqua (eau), caprylic/capric triglyceride, aloe barbadensis leaf juice, polyglyceryl-3 polyricinoleate, glycerin, simmondsia chinensis (jojoba) seed oil, hydrogenated castor oil, sorbitan sesquioleate, hydrogenated methyl abietate, stearyl/octyldodecyl citrate crosspolymer, magnesium sulfate, cucumis sativus (cucumber) extract, malus domestica fruit cell culture extract, helianthus annuus (sunflower) seed oil, sodium hyaluronate, crithmum maritimum extract, crambe maritima leaf extract, vitis vinifera (grape) fruit cell extract, isomalt, lecithin, tremella fuciformis polysaccharide, dextran, caprooyl tetrapeptide-3, copper tripeptide-1, jojoba esters, polyglyceryl-6 polyricinoleate, fragrance (parfum), iron oxides (CI 77492), silica, caprylhydroxamic acid, glyceryl caprylate, ethylhexylglycerin, xanthan gum, sodium benzoate, iron oxides (CI 77491), iron oxides (CI 77499).

Other information

Protect this product from excessive heat & direct sun.

Questions or comments?

https://support.pacificabeauty.com/en-US/contact

Pacifica Beauty LLC Carpinteria, CA 93013